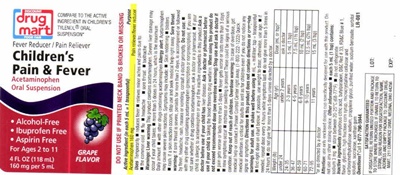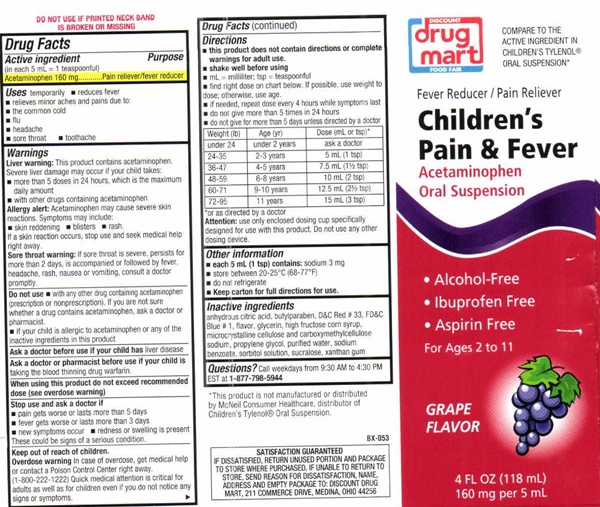 DRUG LABEL: Childrens Pain and Fever
NDC: 53943-526 | Form: LIQUID
Manufacturer: Discount Drug Mart
Category: otc | Type: HUMAN OTC DRUG LABEL
Date: 20251226

ACTIVE INGREDIENTS: ACETAMINOPHEN 160 mg/5 mL
INACTIVE INGREDIENTS: ANHYDROUS CITRIC ACID; BUTYLPARABEN; D&C RED NO. 33; FD&C BLUE NO. 1; GLYCERIN; HIGH FRUCTOSE CORN SYRUP; MICROCRYSTALLINE CELLULOSE; CARBOXYMETHYLCELLULOSE SODIUM; PROPYLENE GLYCOL; WATER; SODIUM BENZOATE; SORBITOL; SUCRALOSE; XANTHAN GUM

Children's Pain & Fever 526

Drug Facts Active ingredient (in each 5 mL = 1 teaspoonful)

Acetaminophen 160 mg

Purpose

Pain reliever/fever reducer

Uses

temporarily

- reduces fever
- relieves minor aches and pains due to:
- the common cold
- flu
- headache
- sore throat
- toothache

Warnings

Liver warning: This product contains acetaminophen.
Severe liver damage may occur if your child takes:

- more than 5 doses in 24 hours, which is the maxium daily amount
- with other drugs containing acteaminophen

Allergy alert: Acetaminophen may cause severe skin reactions. Symptoms may include

- skin reddening
- blisters
- rash

If a skin reaction occurs, stopuse and seek medical help right away.

Sore throat warning: If a sore throat is severe, persiss for more than 2 days, is accompanied or followed by fever, headache, rash, nausea or vomiting, consult a doctor promptly.

Do not use

- with any other drug containing acetaminophen (prescription or nonprescription). If you are not sure whether a drug contains acetaminophen, ask a doctor or pharmacist.
- if your child is allergic to acetaminophen or to any of the inactive ingredients in this product

Ask a doctor if your child has

liver disease

Ask a doctor or pharmacist before use if your child is

taking the blood thinning drug warfarin.

When using this product do not exceed recommended dose.

(see overdose warnings)

Stop use and ask a doctor if

- pain gets worse or lasts more than 5 days
- fever gets worse or lasts more than 3 days
- new symptoms occur
- redness or swelling is present

These could be signs of a serious condition.

Keep out of reach of children.

Overdose warning

In case of overdose, get medical help or contact a Poison Control Center right away. (1-800-222-1222) Quick medical attention is critical for adults as well as for children even if you do not notice any signs or symptoms.

Directions

- this product does not contain directions or complete warnings for adult use.
- shake well before using
- mL = millititer; tsp = teaspoonful
- find right dose on chart below. If possible, use weight to dose, otherwise, use age.
- if needed, repeat dose every 4 hours while symptoms last
- do not give for more than 5 days unless directed by a doctor

Weight (lb) Age (yr) Dose (mL or Tsp)*
under 24 under 2 years ask a doctor

24-35 2-3 years 5 mL (1 tsp)

36-47 4-5 years 7.5 mL (1 1/2 tsp)

48-59 6-8 years 10 mL (2 tsp)

60-71 9-10 years 12.5 mL (2 1/2 tsp)

72-95 11 years 15 mL

* or as directed by a doctor

Attention: use only enclosed dosing cup specfically designed for use with this product. Do not use any other dosing dvice

Other information

- eash 5mL (1 tsp) contains sodium 3mg
- store between 20-25

Inactive ingrediants

anhydrous citric acid, butylparaben, D&C Red # 33, FD&C (red), flavor, glycerin, flavor, high frucotose corn syrup, microcrystalline cellulose and carboxymethylcellulose sodium, propylene glycol, purified water, sodium benzoate, sorbitol solution, sucralose, xanthan gum

Questions

Call weekays from 9:30 AM to 4:30 PM

Children's Pain & Fever product label

DISCOUNT
drug mart
FOOD FAIR

COMPARE TO THE ACTIVE INGREDIENT IN CHILDREN'S TYLENOL® ORAL SUSPENSION

Fever Reducer / Pain Reliever

Children's Pain & Fever

Acetaminophen Oral Suspension

- Alcohol-Free
- Ibuprofen Free
- Aspirin Free

For Ages 2 to 11

GRAPE FLAVOR

4 FL OZ (118 mL)
160 mg per 5 mmL

* This product is not manufactures or distributed by McNeil Consumer Healthcare, distribbutor of Children's Tylenol® Oral Suspension.

BX-053

SATISFACTION GUARANTEED

IF DISSATISFIED, RETURN THE UNUSED PORTION AND PACKAGE TO STORE WHERE PURCHASED. IF UNABLE TO RETURN TO STOORE, SEND REASON FOR DISSATISFACTION, NAME, ADDRESS, AND EMPTY PACKAGE TO: DISCOUNT DRUG MART, 211 COMMERCE DRIVE, MEDINA, OHIO 44256

res